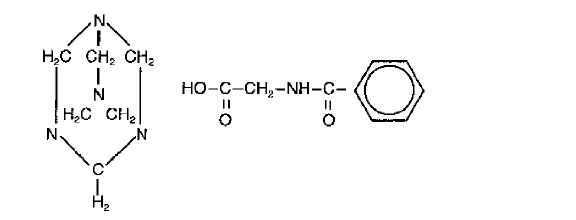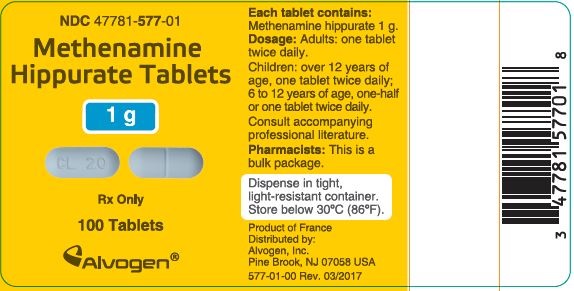 DRUG LABEL: Methenamine Hippurate
NDC: 47781-577 | Form: TABLET
Manufacturer: Alvogen Inc.
Category: prescription | Type: HUMAN PRESCRIPTION DRUG LABEL
Date: 20241117

ACTIVE INGREDIENTS: METHENAMINE HIPPURATE 1 g/1 1
INACTIVE INGREDIENTS: MAGNESIUM STEARATE; POVIDONE, UNSPECIFIED; SACCHARIN SODIUM

Methenamine Hippurate Tablets 1 g

To reduce the development of drug-resistant bacteria and maintain the effectiveness of Methenamine Hippurate Tablets and other antibacterial drugs, Methenamine Hippurate Tablets should be used only to treat or prevent infections that are proven or strongly suspected to be caused by bacteria.

DESCRIPTION

Methenamine Hippurate Tablets are a urinary tract antiseptic drug. Each white, scored tablet contains methenamine hippurate 1g (see HOW SUPPLIED). Methenamine Hippurate Tablets also contain: magnesium stearate, povidone and saccharin sodium. Chemically, methenamine hippurate is the hippuric acid salt of methenamine (hexamethylenetetramine).

Structural formula:

C15H21N5O3

Molecular Weight 319.37

CLINICAL PHARMACOLOGY

Methenamine hippurate is readily absorbed from the GI tract. Methenamine distributes widely into body fluids, but very little is hydrolyzed prior to excretion in the kidney and thus has minimal systemic toxic potential.

Within one-half hour after a single 1 g dose of a Methenamine Hippurate Tablet, antibacterial activity is demonstrable in the urine. Urine shows continuous antibacterial activity when Methenamine Hippurate Tablets are administered at the recommended dosage schedule of 1 g twice daily. Over 90% of the methenamine moiety is excreted in the urine within twenty-four hours after administration of a single 1 g dose. Similarly, the hippurate moiety is rapidly absorbed and excreted, and it reaches the urine by both tubular secretion and glomerular filtration. This may be of importance in older patients or those with some degree of renal impairment.

Methenamine is placentally transferred to the fetus during pregnancy.

Microbiology: Methenamine hippurate exerts its activity because the methenamine component is hydrolyzed to formaldehyde in acid urine. Hippuric acid, the other component, acts to keep the urine acid. The minimal inhibitory concentrations are significantly lower in more acidic media; therefore, the efficacy of Methenamine Hippurate Tablets can be increased by acidification of urine (see DOSAGE AND ADMINISTRATION).

Microorganisms do not develop resistance to formaldehyde; however urea-splitting microorganisms (e.g. Proteus species) tend to raise the pH of the urine thus inhibiting the release of formaldehyde. When the urine pH is 6 and the daily urine volume is 1000 -1500 mL a 2 g dose of Methenamine Hippurate Tablets daily will yield a urinary concentration of 18 to 60 μg/mL of formaldehyde, this being more than the minimal inhibitory concentration for most urinary pathogens.

INDICATIONS AND USAGE

To reduce the development of drug-resistant bacteria and maintain the effectiveness of Methenamine Hippurate Tablets and other antibacterial drugs, Methenamine Hippurate Tablets should be used only to treat or prevent infections that are proven or strongly suspected to be caused by susceptible bacteria. When culture and susceptibility information are available, they should be considered in selecting or modifying antibacterial therapy. In the absence of such data, local epidemiology and susceptibility patterns may contribute to the empiric selection of therapy.

Methenamine Hippurate Tablets are indicated for prophylactic or suppressive treatment of frequently recurring urinary tract infections when long-term therapy is considered necessary. This drug should only be used after eradication of the infection by other appropriate antimicrobial agents.

CONTRAINDICATIONS

Methenamine Hippurate Tablets are contraindicated in patients with renal insufficiency, severe hepatic insufficiency, or severe dehydration. It should not be used as the sole therapeutic agent in acute parenchymal infections causing systemic symptoms.

WARNINGS

Patients with pre-existing hepatic insufficiency may suffer adverse effects from the small amounts of ammonia and formaldehyde that are produced. The classical syndrome of acute hepatic failure may be evoked in these patients.

PRECAUTIONS

General:

Prescribing Methenamine Hippurate Tablets in the absence of a proven or strongly suspected bacterial infection or a prophylactic indication is unlikely to provide benefit to the patient and increases the risk of the development of drug-resistant bacteria.

Large doses of methenamine (8 g daily for 3 to 4 weeks) have caused bladder irritation, painful and frequent micturition, albuminuria and gross hematuria.

Care should be taken to maintain an acid pH of the urine especially when treating infections due to urea-splitting organisms such as Proteus spp. and strains of Pseudomonas spp.

Information for Patients:

Patients should be counseled that antibacterial drugs including Methenamine Hippurate Tablets should only be used to treat bacterial infections. They do not treat viral infections (e.g. the common cold). When Methenamine Hippurate Tablets are prescribed to treat a bacterial infection, patients should be told that although it is common to feel better early in the course of therapy, the medication should be taken exactly as directed. Skipping doses or not completing the full course of therapy may (1) decrease the effectiveness of the immediate treatment and (2) increase the likelihood that bacteria will develop resistance and will not be treatable by Methenamine Hippurate Tablets or other antibacterial drugs in the future.

Laboratory Tests:

In a few instances in one study, the serum transaminase levels showed a mild elevation during treatment which returned to normal while the patients were still receiving Methenamine Hippurate Tablets. Because of this one report, it is recommended that liver function studies be performed periodically on patients receiving the drug, especially those with liver dysfunction.

Drug Interactions:

The concomitant administration of methenamine hippurate and sulfamethizole or sulfathiazole is liable to result in the formation of a precipitate in the urine.

Drug/Laboratory Test Interactions:

Methenamine causes spuriously elevated urinary 17-hydroxycorticosteroid and catecholamine levels.

Carcinogenesis, Mutagenesis and Impairment of Fertility:

Methenamine Hippurate Tablets have not been evaluated for carcinogenicity or mutagenicity.

Methenamine was evaluated for mutagenicity in the Ames Salmonella/mammalian microsome test. Five strains of Salmonella typhimurium (TA98, TA100, TA1535, TA1537 and TA1538) and a strain of Escherichia coli (WP2uvrA) were used. At a dose of 10,000 μg/plate methenamine showed mutagenic activity in Salmonella typhimurium TA98 and TA100 by metabolic activation and also showed mutagenic activity in TA98 without microsomal activation.

In one large study, no evidence of carcinogenicity was found following long-term oral administration of methenamine 1.25g/kg/day to rats (104 weeks) and mice (60 weeks). The same investigators also reported no suggestion of carcinogenicity resulting from five subcutaneous injections of 5 g/kg (given on alternate days for a total dose of 25 g/kg). An earlier, much smaller study showed a 50% incidence of local sarcomas following subcutaneous injection of methenamine, totaling 25 g/kg, administered over periods of up to 15 months to rats concurrently receiving formic acid.

Methenamine hippurate, administered at a dose level of 800 mg/kg/day, did not adversely affect the fertility of female rats. Effects on male fertility have not been adequately studied.

Pregnancy:

Teratogenic effects. Pregnancy category C. Oral administration of methenamine to pregnant dogs, at doses equivalent to the human dose, has been reported to cause a slight increase in the stillborn rate and slight impairment of weight gain and survival of live-born offspring. A teratogenicity study, in which methenamine hippurate was administered to pregnant rabbits at doses approximately 3 times human dose, revealed no evidence of harm to the fetus. There are no adequate and well-controlled studies in pregnant women. Methenamine Hippurate Tablets should be used during pregnancy only if the potential benefit justifies the potential risk to the fetus.

Labor and Delivery:

Methenamine Hippurate Tablets have no recognized use during labor and delivery, and their effect during these processes is unknown.

Nursing Mothers:

Methenamine is excreted in human milk. Because of the potential for serious adverse reactions in nursing infants, a decision should be made whether to discontinue nursing or to discontinue the drug, taking into account the importance of the drug to the mother.

Pediatric Use:

(see DOSAGE AND ADMINISTRATION).

ADVERSE REACTIONS

Adverse effects of Methenamine Hippurate Tablets have been reported in fewer than 3.5% of patients treated.

These reactions have included the following, in decreasing order of frequency: nausea, vomiting and rarely pruritus, rash, dysuria.

Children have received Methenamine Hippurate Tablets at the recommended dosages as a prophylactic/suppressive regimen after initial treatment of acute episodes of pyuria. Side effects were encountered in only 1.1% of these children.

OVERDOSAGE

Immediately after ingestion of an overdose, further absorption of the drug may be minimized by inducing vomiting or by gastric lavage, followed by administration of activated charcoal. Fluids, either oral or parenteral, should be forced to tolerance.

DOSAGE AND ADMINISTRATION

One tablet (1 g) twice daily for adults and children over 12 years of age. One-half tablet or one tablet (0.5 or 1 g) twice daily for children 6 to 12 years of age.

The antibacterial activity of Methenamine Hippurate Tablets is greater in acid urine. Therefore, restriction of alkalinizing foods and medications is desirable. If necessary, as indicated by urinary pH and clinical response, supplemental acidification of the urine may be instituted. The efficacy of therapy should be monitored by repeated urine cultures.

HOW SUPPLIED

Methenamine Hippurate Tablets are capsule-shaped, scored, white, debossed “CL 20” on one side. Each tablet contains methenamine hippurate 1 g.

Bottles of 100 tablets (NDC 47781-577-01).

Store at controlled room temperature 15°-30°C (59°-86°F).

ANIMAL PHARMACOLOGY AND ANIMAL TOXICOLOGY

Up to 600 mg/kg of methenamine hippurate in a single dose have been administered intravenously to dogs and to rats without toxic effects being observed. Chronic oral administration of 50 to 200 mg/kg/day to dogs and 800 to 6400 mg/kg/day to rats produced gastric and bladder irritation with some hemorrhagic sites and ulcerations observed at autopsy. Amounts of methenamine hippurate equivalent to twice the recommended human dose were administered to rats for twelve months and to monkeys for six months without producing any adverse effects.

Rx only

Product of France

Distributed by: Alvogen, Inc.
Pine Brook, NJ 07058 USA

For Inquires Call:
1-866-770-3024

PI577-00
Rev. 03/2017

PACKAGE/LABEL PRINCIPAL DISPLAY PANEL

NDC 47781-577-01

Methenamine Hippurate Tablets

1g

Rx only

100 Tablets